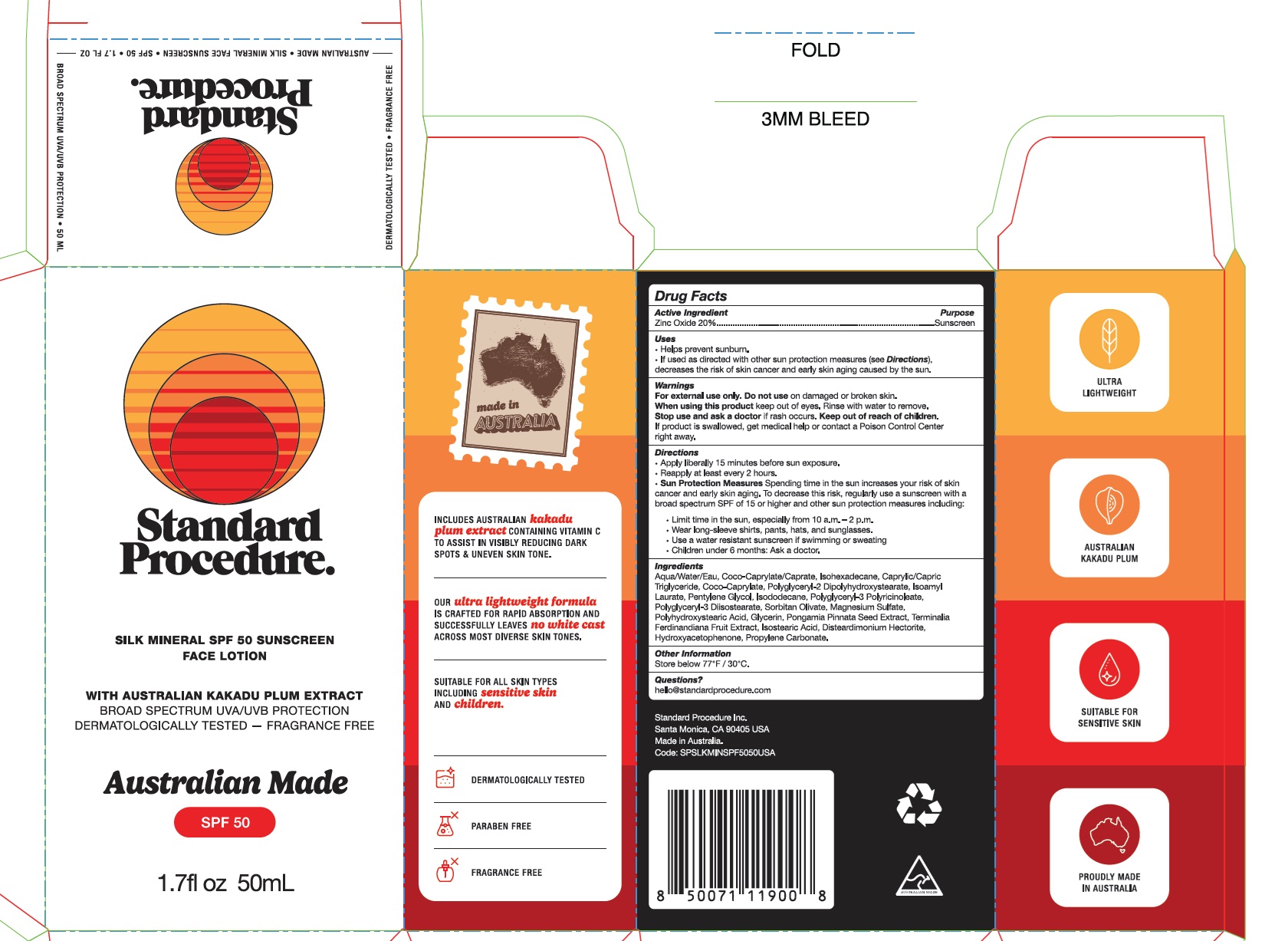 DRUG LABEL: Silk Mineral SPF 50 Sunscreen Face
NDC: 70157-026 | Form: LOTION
Manufacturer: Baxter Laboratories
Category: otc | Type: HUMAN OTC DRUG LABEL
Date: 20250428

ACTIVE INGREDIENTS: ZINC OXIDE 20 g/100 mL
INACTIVE INGREDIENTS: PENTYLENE GLYCOL; POLYHYDROXYSTEARIC ACID (2300 MW); GLYCERIN; KAKADU PLUM; WATER; COCO-CAPRYLATE/CAPRATE; COCO-CAPRYLATE; POLYGLYCERYL-3 PENTARICINOLEATE; CAPRYLIC/CAPRIC TRIGLYCERIDE; POLYGLYCERYL-3 DIISOSTEARATE; PROPYLENE CARBONATE; ISODODECANE; DISTEARDIMONIUM HECTORITE; HYDROXYACETOPHENONE; PONGAMIA PINNATA SEED; ISOSTEARIC ACID; ISOAMYL LAURATE; ISOHEXADECANE; SORBITAN OLIVATE; MAGNESIUM SULFATE; POLYGLYCERYL-2 DIPOLYHYDROXYSTEARATE

Standard Procedure Silk Mineral SPF 50 Sunscreen Face Lotion

Active Ingredient Purpose

Zinc Oxide20%....Sunscreen

Uses

- Helps prevent sunburn
- If used as directed with other sun protection measures (see Directions), decreases the risk of skin cancer and early skin aging caused by the sun.

Keep out of reach of children. If product is swallowed, get medical help or contact a poison control center right awa.

Stop use and ask a doctor if rash occurs.

Warnings

For external use only. Do not use on damaged or broken skin

When using this product keep out of eyes. Rinse with water to remove.

Directions

Apply liberally 15 minutes before sun exposure

Reapply at least every 2 hours

INACTIVE INGREDIENT

Ingredients

Aqua/Water/Eau, Coco-Caprylate/Caprate, Isohexadecane, Caprylic/Capric Triglyceride, Coco-Caprylate, Polyglyceryl-2 Dipolyhydroxystearate, Isoamyl Laurate, Pentylene Glycol, Isododecane, Polyglyceryl-3 Polyricinoleate, Polyglyceryl-3 Diisostearate, Sorbitan Olivate, Magnesium Sulfate, Polyhydroxystearic Acid, Glycerin, Pongamia Pinnata Seed Extract, Terminalia Ferdinandiana Fruit Extract, Isostearic Acid, Disteardimonium Hectorite, Hydroxyacetophenone, Propylene Carbonate

PACKAGE LABEL

Standard Procedure

Silk Mineral SPF 50 Sunscreen Face Lotion

1.7 fl oz 50 mL